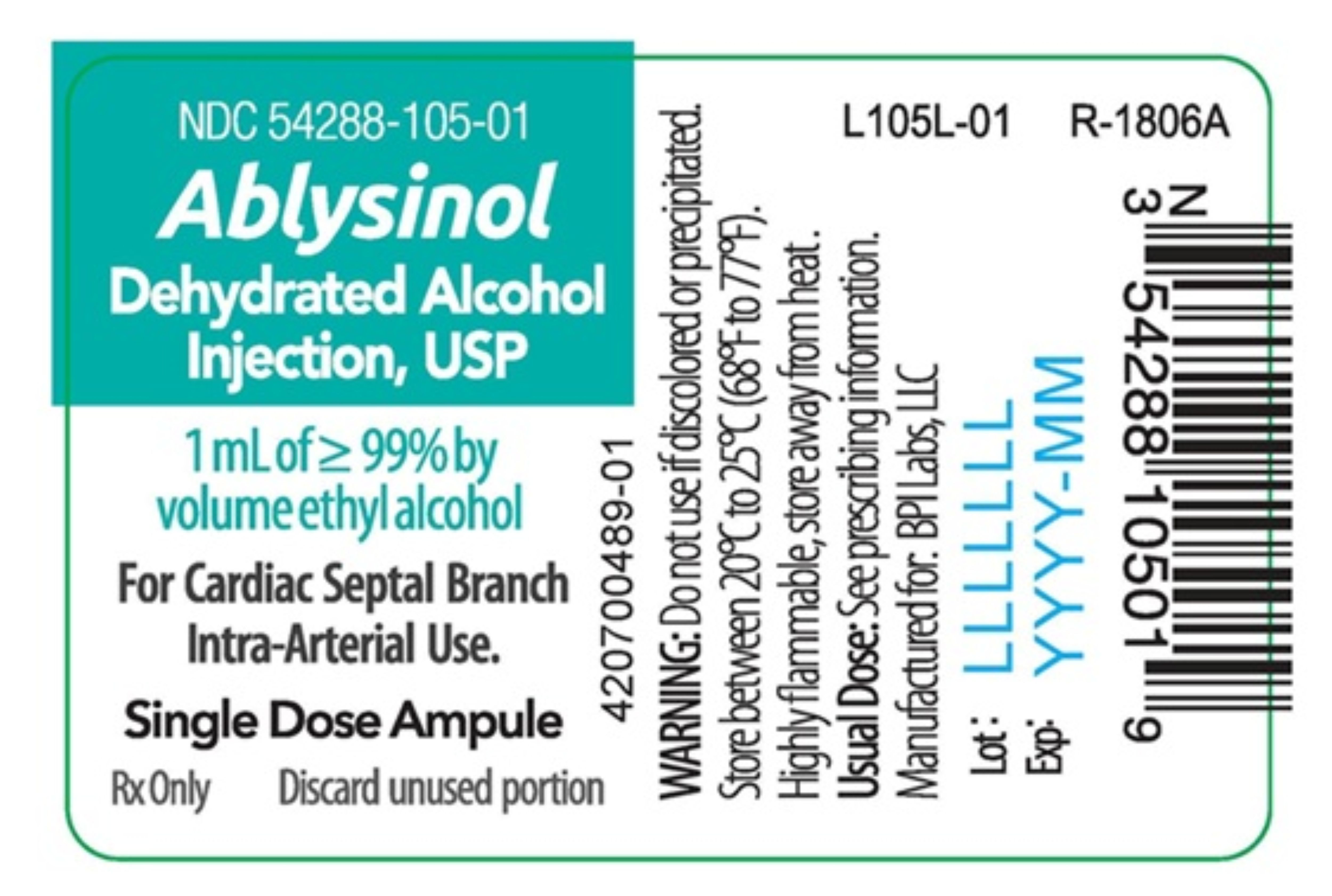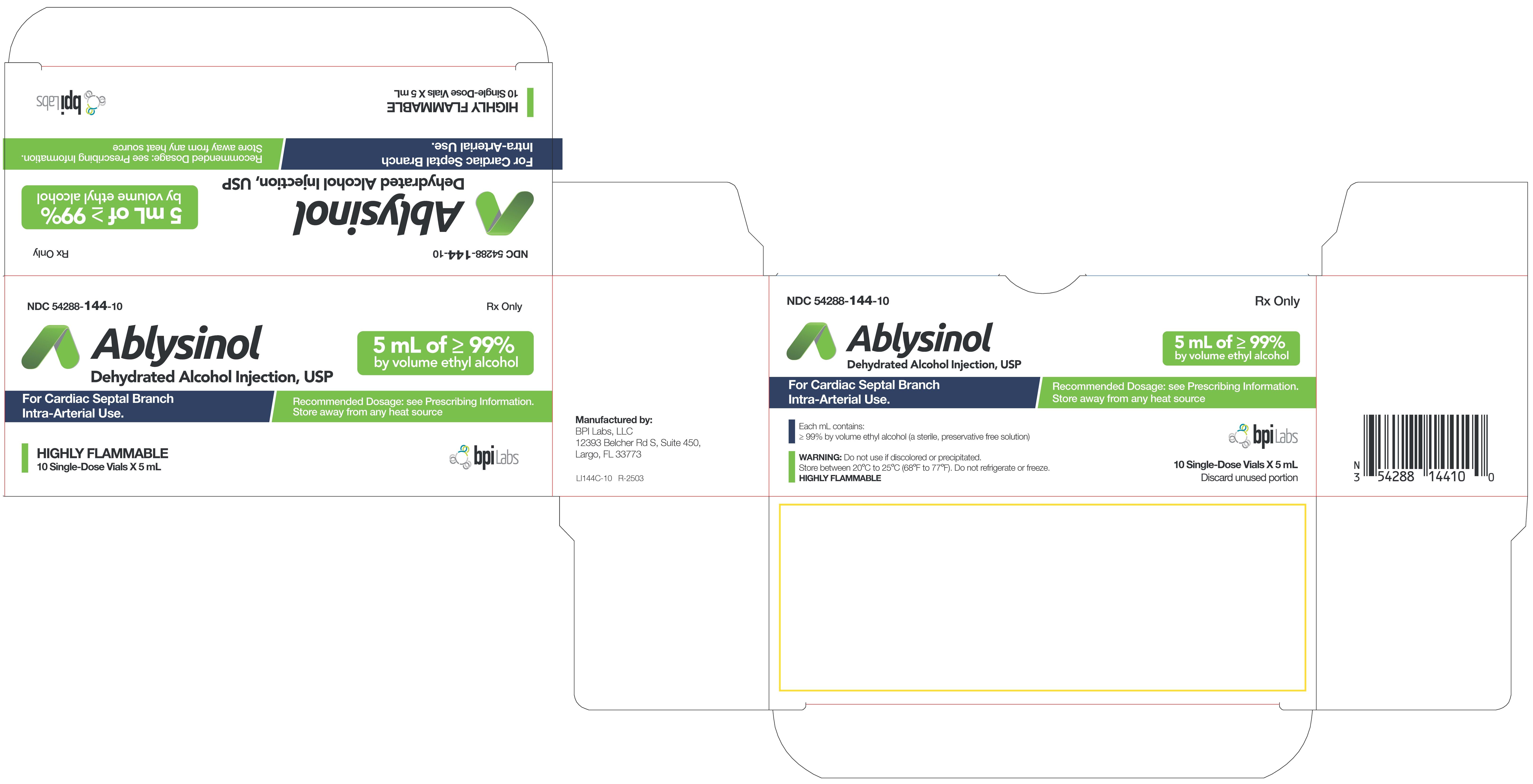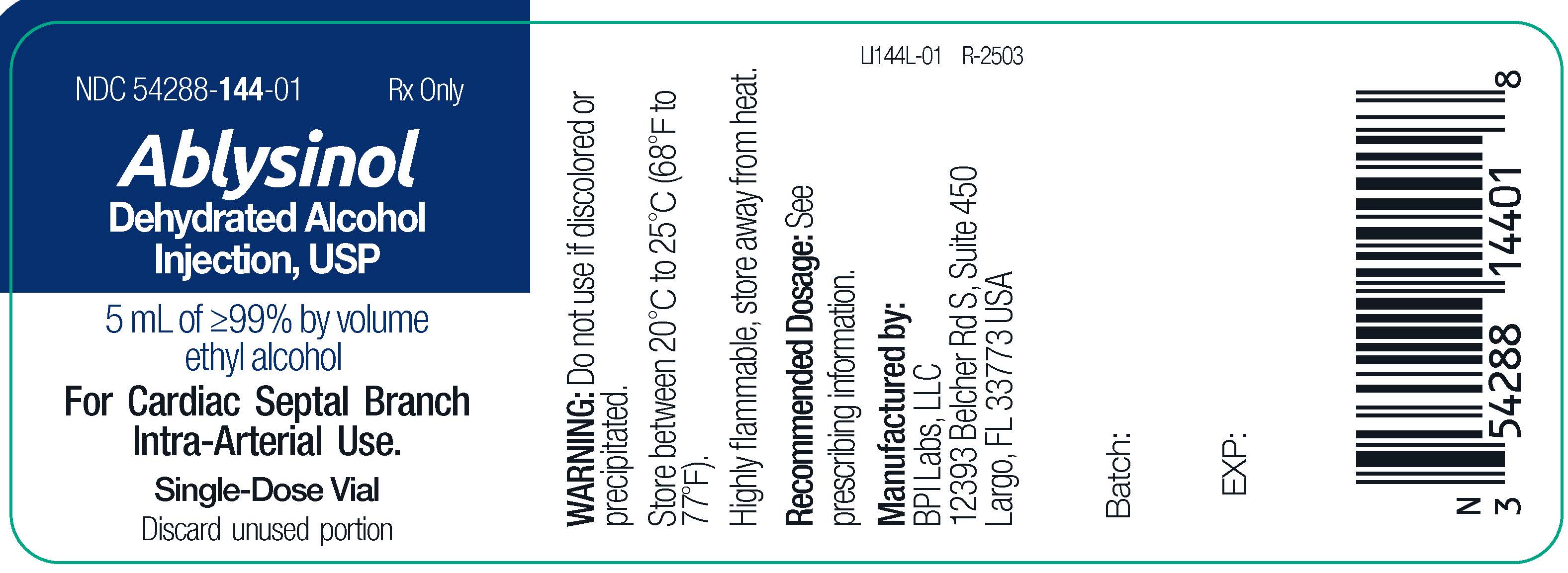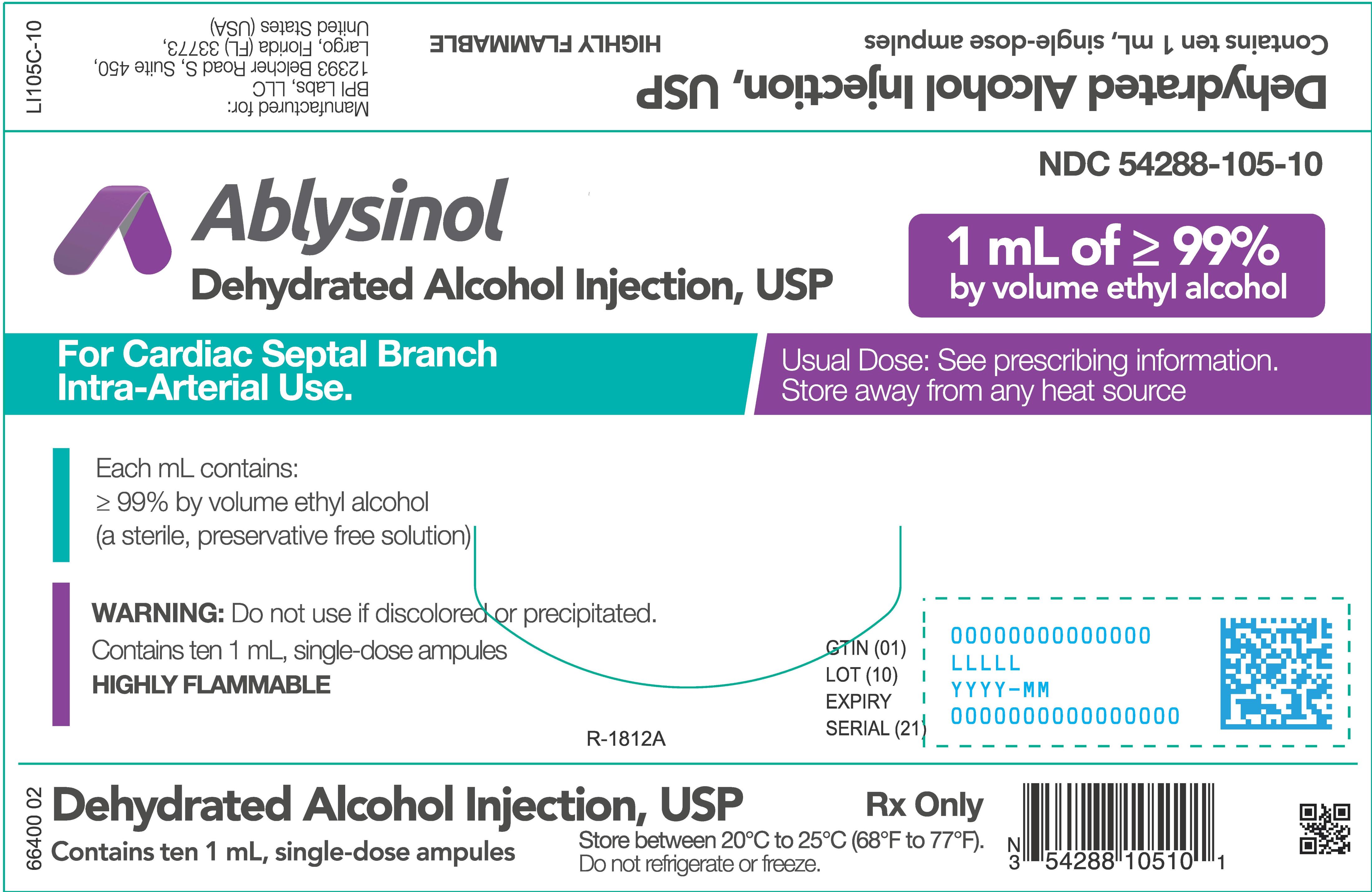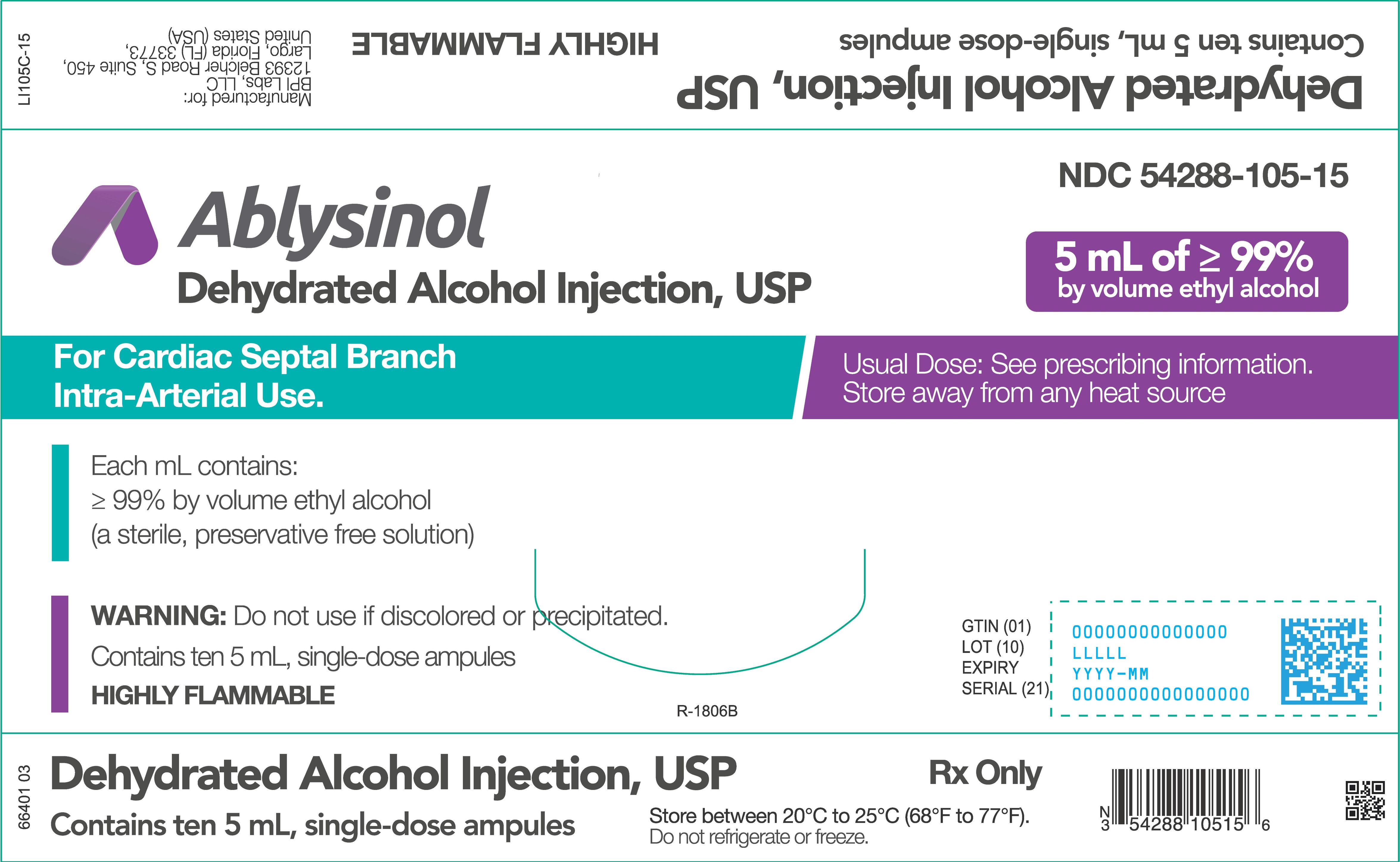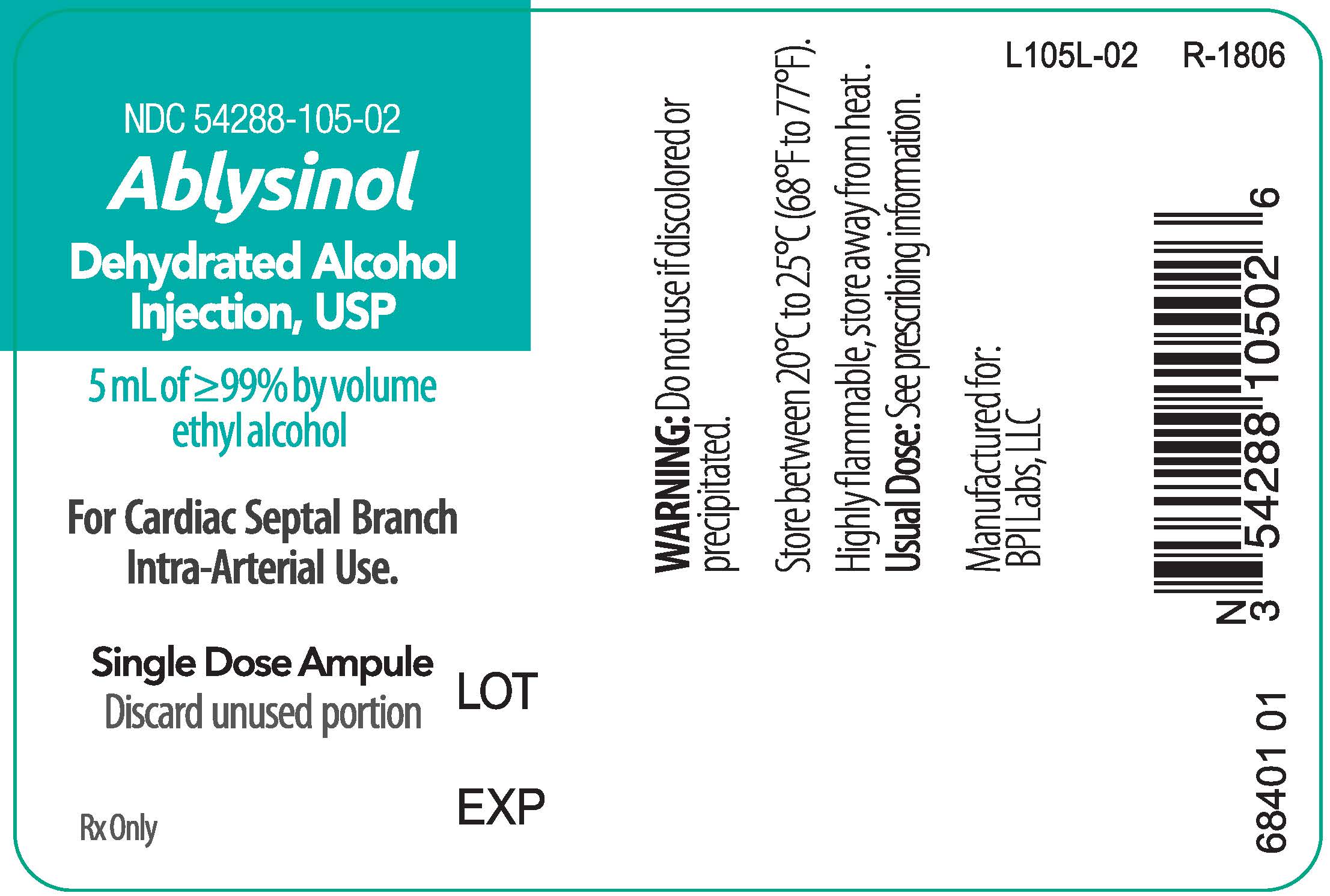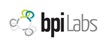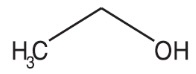 DRUG LABEL: Dehydrated Alcohol
NDC: 54288-105 | Form: INJECTION, SOLUTION
Manufacturer: BPI Labs, LLC
Category: prescription | Type: HUMAN PRESCRIPTION DRUG LABEL
Date: 20260105

ACTIVE INGREDIENTS: ALCOHOL 1 mL/1 mL

HIGHLIGHTS OF PRESCRIBING INFORMATION

These highlights do not include all the information needed to use ABLYSINOL® safely and effectively. See full prescribing information for ABLYSINOL.
ABLYSINOL (dehydrated alcohol) injection, for cardiac septal branch intra-arterial use
Initial U.S. Approval: 1946

1 INDICATIONS AND USAGE

ABLYSINOL is an ablative agent indicated to induce controlled cardiac septal infarction to improve exercise capacity in adults with symptomatic hypertrophic obstructive cardiomyopathy who are not candidates for surgical myectomy. (1)

2 DOSAGE AND ADMINISTRATION

- Inject small volumes over 1 to 2 minutes percutaneously into septal arterial branches, using the minimal dose necessary to achieve the desired reduction in peak left ventricular outflow tract pressure gradient. (2.1)
- In most situations, a dose of 1 mL to 2 mL is sufficient. The maximum dose that should be used in a single procedure is 5 mL. (2.1)

3 DOSAGE FORMS AND STRENGTHS

- Injection: 1 mL or 5 mL of ethyl alcohol ≥ 99% by volume as a clear, colorless liquid in a single-dose glass ampule. (3)
- Injection: 5 mL of ethyl alcohol ≥ 99% by volume as a clear, colorless liquid in a single-dose glass vial. (3)

4 CONTRAINDICATIONS

- None (4)

5 WARNINGS AND PRECAUTIONS

- Transient heart block: Transient heart block is common at the time of injection. A temporary pacing wire is routinely inserted to mitigate transient heart block. (5.1)
- Persistent heart block: Approximately 10% of complete heart block events become permanent and require placement of a permanent pacemaker. (5.1)
- Remove the temporary pacemaker lead if no episode of high-degree atrioventricular block occurs. (5.1)
- Monitor the patient for heart failure, chest pain, and arrhythmias several days after the procedure. (5.1, 5.2, 5.3)

6 ADVERSE REACTIONS

Adverse reactions include arrhythmias, including ventricular tachycardia and/or ventricular fibrillation. (6)

To report SUSPECTED ADVERSE REACTIONS, contact BPI Labs, LLC at (727) 471-0850 or FDA at 1-800-FDA-1088 or www.fda.gov/medwatch.

8 USE IN SPECIFIC POPULATIONS

- ABLYSINOL is not recommended during pregnancy. Maternal use is not expected to result in fetal exposure to the drug. (8.1)
- The rate of heart blocks and dysrhythmia increased with age. (8.5)

See 17 for PATIENT COUNSELING INFORMATION

FULL PRESCRIBING INFORMATION

1 INDICATIONS AND USAGE

ABLYSINOL® is indicated to induce controlled cardiac septal infarction to improve exercise capacity in adults with symptomatic hypertrophic obstructive cardiomyopathy who are not candidates for surgical myectomy.

2 DOSAGE AND ADMINISTRATION

2.1 Recommended Dosing

Use the minimum dose necessary to achieve the desired reduction in peak left ventricular outflow tract pressure gradient. Inject small volumes over 1 to 2 minutes percutaneously into septal arterial branches, guided by assessment of the gradient. In most situations, a dose of 1 mL to 2 mL is sufficient. The maximum dose of ABLYSINOL that should be used in a single procedure is 5 mL.

2.2 Administration

ABLYSINOL should only be administered under the supervision of a qualified interventional cardiologist experienced in the percutaneous transluminal septal myocardial ablation procedure.

Inspect visually for particulate matter and discoloration prior to administration. ABLYSINOL should appear as a clear, colorless solution.

3 DOSAGE FORMS AND STRENGTHS

Injection: 1 mL or 5 mL of ethyl alcohol ≥ 99% by volume as a clear, colorless liquid in a single-dose glass ampule.

Injection: 5 mL of ethyl alcohol ≥ 99% by volume as a clear, colorless liquid in a single-dose glass vial.

4 CONTRAINDICATIONS

None.

5 WARNINGS AND PRECAUTIONS

5.1 Heart Block

Transient Heart Block
Transient heart block is common at the time of dehydrated alcohol, such as ABLYSINOL, injection into a septal artery. Prior to the injection, a temporary pacing wire is routinely inserted into the apex of the right ventricle, usually via the femoral vein, to treat transient heart block. The pacing lead can be removed if no episode of high-degree atrioventricular block occurs, usually after several hours of observation following percutaneous transluminal septal myocardial ablation.

Persistent Heart Block
Approximately 10% of complete heart block events become permanent and require placement of a permanent pacemaker following percutaneous transluminal septal myocardial ablation. Risk factors for permanent pacemaker dependency after septal ablation include a baseline PQ interval > 160 ms, baseline minimum heart rate < 50 bpm, baseline left ventricular outflow gradient > 70 mmHg, maximum QRS during the first 48 hours > 155 ms, 3rd degree atrio-ventricular block occurring during the procedure, and no clinical recovery between 12-48 hours after the procedure.

5.2 Myocardial Infarction

Injection of dehydrated alcohol is intended to create a controlled myocardial infarction for therapeutic purposes. However, excessive myocardial necrosis and subsequent heart failure have been reported. Factors increasing the risk of excessive tissue necrosis include higher volume of alcohol used and a higher number of septal branches injected to reduce the left ventricular outflow tract gradient.

5.3 Ventricular Arrhythmia

Ventricular tachycardia and ventricular fibrillation requiring electrocardioversion occurred at a frequency of approximately 1%. Perform continuous electrocardiographic monitoring for 48 hours after the procedure.

6 ADVERSE REACTIONS

Heart block [ see Warnings and precautions (5.1)]

The following other adverse reactions associated with percutaneous transluminal septal myocardial ablation with the use of dehydrated alcohol, such as ABLYSINOL, were identified in the literature: Ventricular tachycardia and ventricular fibrillation.

8 USE IN SPECIFIC POPULATIONS

8.1 Pregnancy

Risk Summary
The concentrations of alcohol in blood after PTSMA were not measured, but ABLYSINOL is not expected to increase significantly the systemic concentrations of endogenous alcohol following administration into a septal artery during percutaneous transluminal septal myocardial ablation. Maternal use is not expected to result in fetal exposure to the drug.

Clinical Considerations
ABLYSINOL for percutaneous transluminal septal myocardial ablation has not been evaluated in pregnant women and is not recommended during pregnancy. When possible, the percutaneous transluminal septal myocardial ablation procedure should be postponed in women until the postpartum period.

Data
Animal reproduction studies have shown an adverse effect on the fetus and chronic fetal alcohol exposure is known to cause developmental defects in human. The developmental effects of acute ethanol exposure, such as from percutaneous transluminal septal myocardial ablation, have not been studied in pregnant or lactating women.

8.2 Lactation

ABLYSINOL is not expected to increase significantly the systemic concentrations of endogenous alcohol following administration into a septal artery during percutaneous transluminal septal myocardial ablation and breastfeeding is not expected to result in exposure of the child to the drug.

8.4 Pediatric Use

Safety and effectiveness in pediatric patients have not been established.

8.5 Geriatric Use

A comparison of the outcomes in patients with hypertrophic obstructive cardiomyopathy in patients < 60 years old and in patients ≥ 60 years old showed similar improvement in exercise capacity after ablation. The rate of heart blocks and dysrhythmia increased with age. Permanent pacemaker dependency increased to 34% in patients > 60 years old.

10 OVERDOSAGE

There is a direct correlation between the volume of alcohol and size of iatrogenic myocardial infarction. Stop the procedure if there is failure to reduce the left ventricular outflow tract pressure gradient to less than 10 mmHg when reaching a total dose of 5 mL.

11 DESCRIPTION

ABLYSINOL (dehydrated alcohol) injection is a sterile, preservative free solution of ≥ 99% by volume ethyl alcohol and no excipients. ABLYSINOL is for cardiac septal branch intra-arterial use. It has a molecular formula of C2H6O and a molecular weight of 46.07.

Dehydrated Alcohol Injection, USP is a potent tissue toxin. Ethanol is a clear, colorless, volatile, and flammable liquid miscible with water. It has the following structural formula:

12 CLINICAL PHARMACOLOGY

12.1 Mechanism of Action

Dehydrated alcohol is a tissue toxin that produces a myocardial infarction when injected through an intra-arterial catheter into a target septal vessel, which causes the hypertrophied septum to thin.

12.2 Pharmacodynamics

A dose independent, approximate 70% reduction of the peak pressure gradient across left ventricular outflow tract is observed after injection of alcohol volumes in the range of 1-4 mL. Remodeling contributes about 20% to the 70% total reduction in peak pressure gradient across the left ventricular outflow tract measured 12 months after septal ablation. Other markers, such as infarct size or peak concentration of creatine kinase-MB (CK-MB), in contrast to peak pressure gradient across the left ventricular outflow tract, vary in proportion to the injected alcohol volume in the 1-4 mL range.

12.3 Pharmacokinetics

Because injection of ABLYSINOL during septal ablation is not expected to increase the systemic concentrations of endogenous alcohol significantly, the pharmacokinetics of dehydrated alcohol are not expected to be clinically significant.

13 NONCLINICAL TOXICOLOGY

13.1 Carcinogenesis, Mutagenesis, Impairment of Fertility

Ethanol (of alcohol beverages) was added to Group 1 International Agency for Research on Cancer (IARC) Carcinogenicity Ratings (IARC monographs). Substances in this group are either carcinogenic to humans, or there is sufficient evidence of carcinogenicity in experimental animals and strong evidence in exposed humans that the substance acts through a relevant mechanism of carcinogenicity. Alcohol consumption has been associated with various cancers, including liver, esophageal, breast, prostate, and colorectal cancer. Since ABLYSINOL is not expected to reach the systemic circulation following administration into a septal artery during percutaneous transluminal septal myocardial ablation, the recommended clinical use of the drug product is not expected to have carcinogenic risk in patients.

Literature reports suggest that ethanol is not mutagenic in the in vitro bacterial reverse mutation (Ames) assay or in vitro chromosomal aberration assays. Ethanol is metabolized to acetaldehyde, which is a known mutagen.

There are no data from either animal or human studies regarding potential for the impairment of fertility.

13.2 Animal Toxicology and/or Pharmacology

The median lethal dose (LD50) values for ethyl alcohol given by intravenous and oral routes are 1440 and 7060 mg/kg in rats and 1973 and 3450 mg/kg in mice, respectively. The LD50 for ethyl alcohol given by subcutaneous injection is 8285 mg/kg in mice.

14 CLINICAL STUDIES

Evidence of the effectiveness of ethanol on exercise capacity in adults with symptomatic hypertrophic obstructive cardiomyopathy who are not candidates for surgical myectomy was obtained from literature involving over 4000 patients.

16 HOW SUPPLIED/STORAGE AND HANDLING

ABLYSINOL (dehydrated alcohol) injection is a clear, colorless liquid supplied in clear, glass, single-dose ampules and single-dose vials. Each mL contains 99% by volume ethyl alcohol.

Volume | NDC
 | Single ampule | Carton of 10 ampules
1 mL | 54288-105-01 | 54288-105-10
5 mL | 54288-105-02 | 54288-105-15
 | Single Vial | Carton of 10 Vials
5 mL | 54288-144-01 | 54288-144-10

Store at room temperature, between 20°C and 25°C (68°F and 77°F). Do not refrigerate or freeze. Highly flammable, store away from any heat source.

Ampules:

Manufactured for:

BPI Labs, LLC, Largo, FL 33773 USA

Manufactured by:
Sintetica SA
Via Penate 5
6850 Mendrisio, Switzerland

Vials:

Manufactured by:
BPI Labs, LLC
12393 Belcher Rd S, Suite 450
Largo, FL 33773

PRINCIPAL DISPLAY PANEL - 1 mL AMPULE

ABLYSINOL® (Dehydrated Alcohol Injection, USP)
NDC 54288-105-01
1 mL - AMPULE - LABEL

ABLYSINOL® (Dehydrated Alcohol Injection, USP)
NDC 54288-105-10
1 mL - AMPULE - CARTON - 10 PACK

PRINCIPAL DISPLAY PANEL - 5 mL AMPULE

ABLYSINOL® (Dehydrated Alcohol Injection, USP)

NDC 54288-105-02

5mL - AMPULE - LABEL

ABLYSINOL® (Dehydrated Alcohol Injection, USP)
NDC 54288-105-15
5mL - AMPULE - CARTON - 10 PACK

PRINCIPAL DISPLAY PANEL - 5 mL VIAL

ABLYSINOL® (Dehydrated Alcohol Injection, USP)

NDC 54288-144-01
5 mL - VIAL - LABEL

ABLYSINOL® (Dehydrated Alcohol Injection, USP)
NDC 54288-144-10
5 mL - VIAL - CARTON - 10 PACK